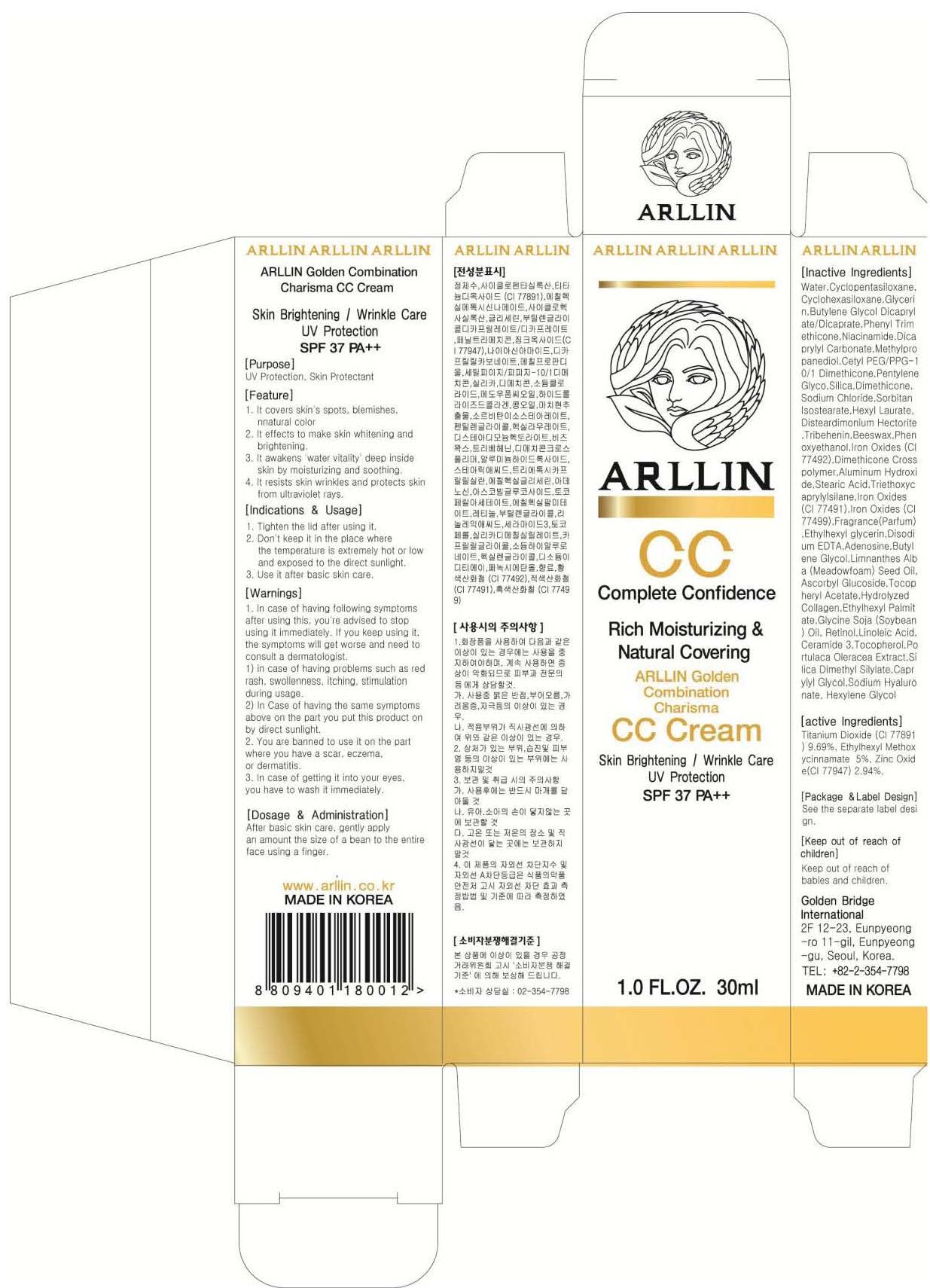 DRUG LABEL: Arllin Golden Combination Charisma CC
NDC: 61315-010 | Form: CREAM
Manufacturer: Golden Bridge International
Category: otc | Type: HUMAN OTC DRUG LABEL
Date: 20130816

ACTIVE INGREDIENTS: Titanium Dioxide 2.90 mg/30 mL; OCTINOXATE 1.50 mg/30 mL; Zinc Oxide 0.88 mg/30 mL
INACTIVE INGREDIENTS: Water; Glycerin

ACTIVE INGREDIENT

Active Ingredients: Titanium Dioxide(CI 77891) 9.69%, Ethylhexyl Methoxycinnamate 5%, Zinc Oxide(CI 77947) 2.94%

INACTIVE INGREDIENT

Inactive Ingredients:
Water,Cyclopentasiloxane,Cyclohexasiloxane, Glycerin, Butylene Glycol Dicaprylate/Dicaprate,Phenyl Trimethicone, Niacinamide, Dicaprylyl Carbonate,Methylpropanediol, Cetyl PEG/PPG-10/1 Dimethicone,Pentylene Glyco,Silica, Dimethicone,Sodium Chloride,Sorbitan Isostearate,
Hexyl Laurate,Disteardimonium Hectorite,Tribehenin, Beeswax,Phenoxyethanol,Iron Oxides (CI 77492), Dimethicone Crosspolymer,Aluminum Hydroxide,Stearic Acid, Triethoxycaprylylsilane,Iron Oxides (CI 77491), Iron Oxides (CI 77499),Fragrance(Parfum),
Ethylhexylglycerin,Disodium EDTA, Adenosine, Butylene Glycol, Limnanthes Alba (Meadowfoam) Seed Oil,Ascorbyl Glucoside, Tocopheryl Acetate,Hydrolyzed Collagen,Ethylhexyl Palmitate, Glycine Soja (Soybean) Oil, Retinol,Linoleic Acid,Ceramide 3,
Tocopherol,Portulaca Oleracea Extract,Silica Dimethyl Silylate, Caprylyl Glycol,Sodium Hyaluronate, Hexylene Glycol

PURPOSE

Purpose: UV Protection, Skin Protectant

WARNINGS

1. In case of having following symptoms after using this, you're advised to stop using it immediately. If you keep using it, the symptoms will get worse and need to consult a dermatologist.
1) in case of having problems such as red rash, swollenness, itching, stimulation during usage.
2) In Case of having the same symptoms above on the part you put this product on by direct sunlight.
2. You are banned to use it on the part where you have a scar, eczema, or dermatitis.
3. In case of getting it into your eyes, you have to wash it immediately.

KEEP OUT OF REACH OF CHILDREN

Keep out of reach of babies and children.

Indications and Usage

1. Tighten the lid after using it.
2. Don't keep it in the place where the temperature is extremely hot or low and exposed to the direct sunlight.
3. Use it after basic skin care.

Dosage and Administration

After basic skin care, gently apply an amount the size of a bean to the entire face using a finger.